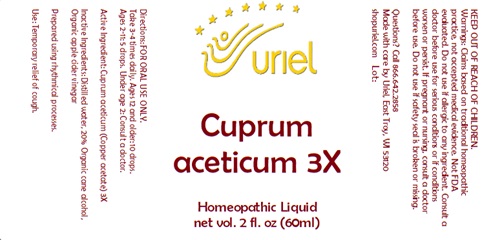 DRUG LABEL: Cuprum Aceticum 3
NDC: 48951-3139 | Form: LIQUID
Manufacturer: Uriel Pharmacy Inc.
Category: homeopathic | Type: HUMAN OTC DRUG LABEL
Date: 20241008

ACTIVE INGREDIENTS: CUPRIC ACETATE 3 [hp_X]/1 mL
INACTIVE INGREDIENTS: WATER; ALCOHOL; APPLE CIDER VINEGAR

Cuprum aceticum 3

INDICATIONS AND USAGE

Directions: FOR ORAL USE ONLY.

DOSAGE AND ADMINISTRATION

Take 3-4 times daily. Ages 12 and older: 10 drops. Ages 2-11: 5 drops. Under age 2: Consult a doctor.

Active Ingredient: Cuprum aceticum 3X

INACTIVE INGREDIENT

Inactive Ingredients: Distilled water, Organic cane alcohol, Organic apple cider vinegar

Prepared using rhythmical processes

PURPOSE

Use: Temporary relief of cough.

KEEP OUT OF REACH OF CHILDREN.

WARNINGS

Warnings: Claims based on traditional homeopathic practice, not accepted medical evidence. Not FDA evaluated. Do not use if allergic to any ingredient. Consult a doctor before use for serious conditions or if conditions worsen or persist. If pregnant or nursing, consult a doctor before use. Do not use if safety seal is broken or missing.

QUESTIONS

Questions? Call 866.642.2858 Made with care by Uriel, East Troy, WI 53120 shopuriel.com Lot: